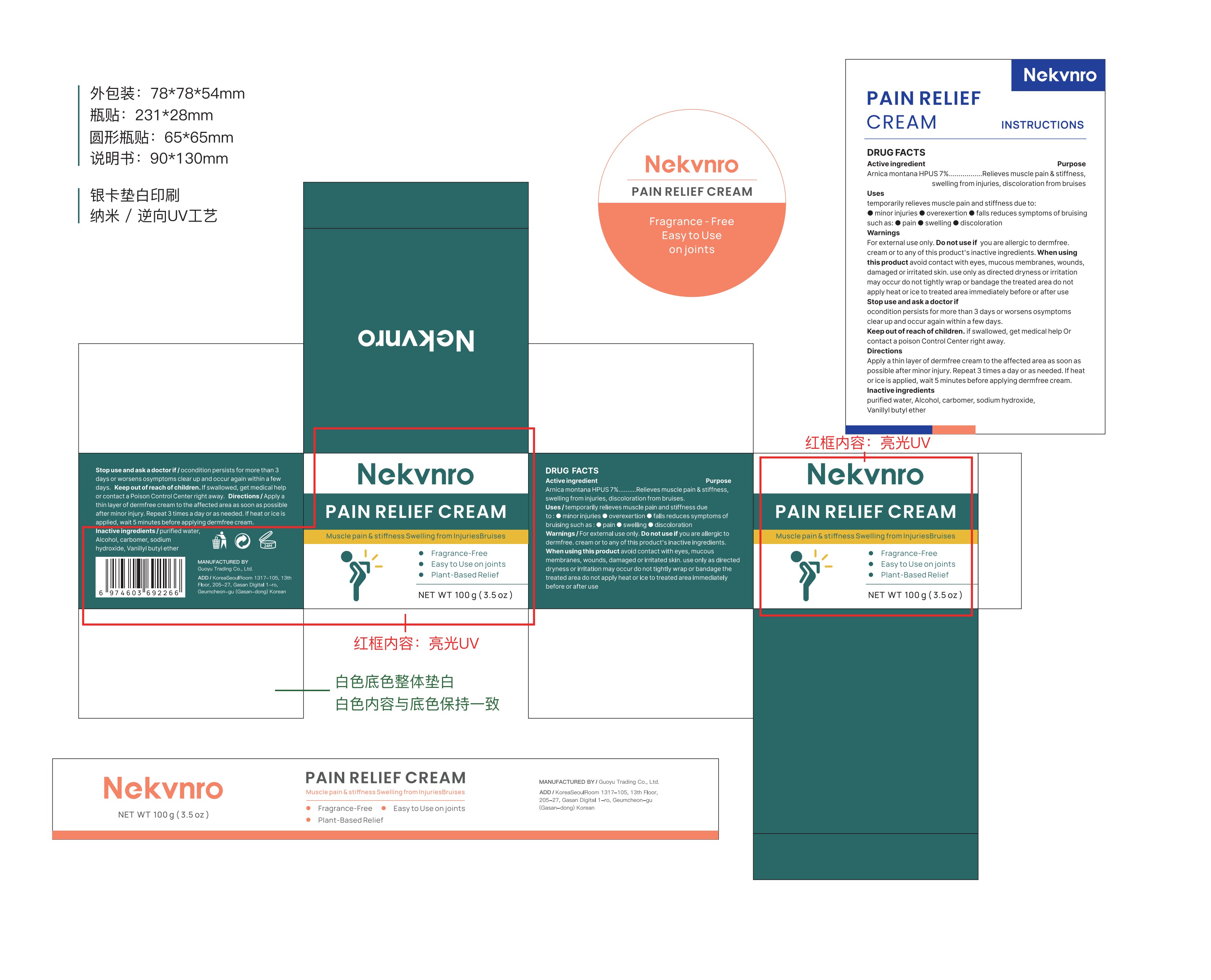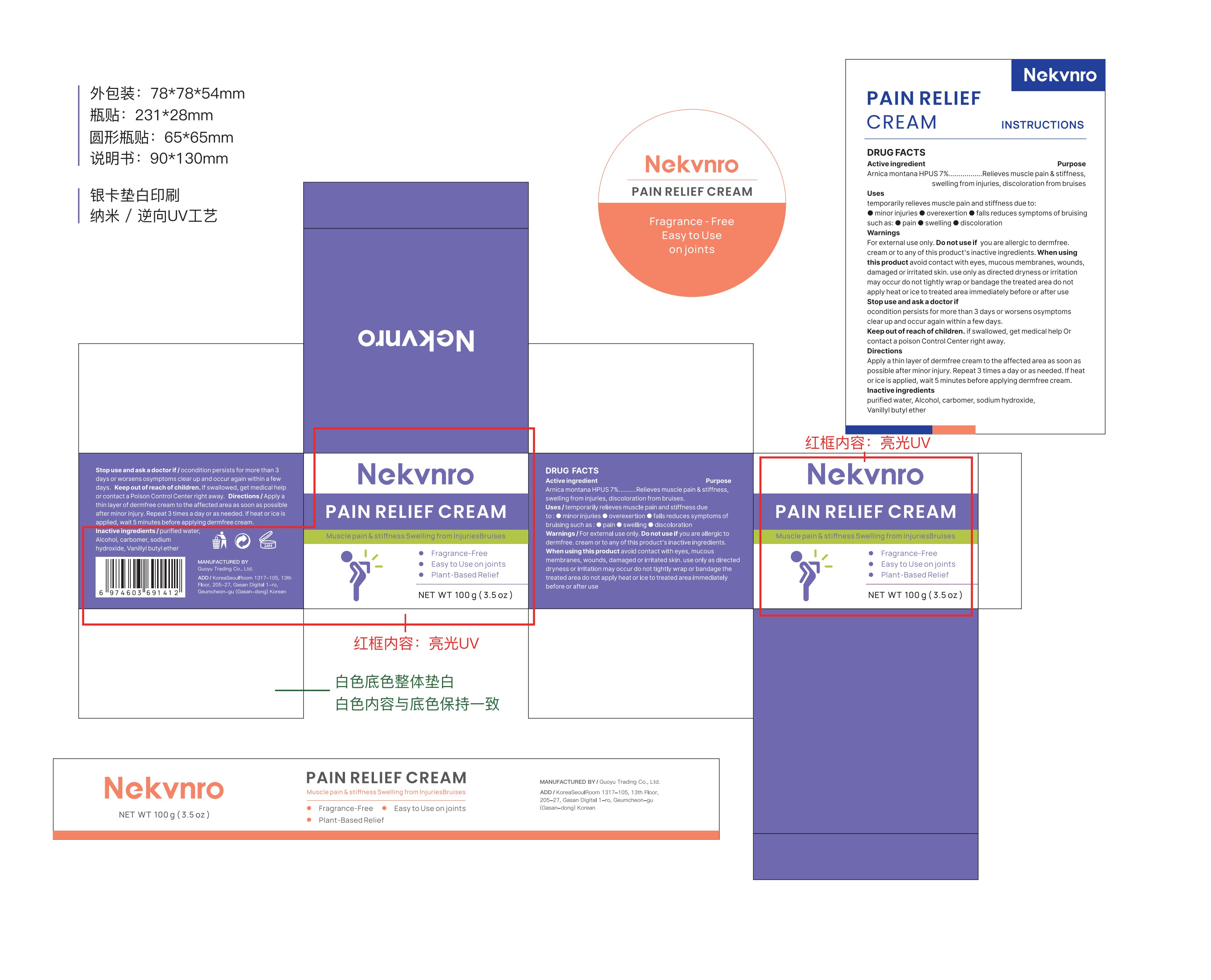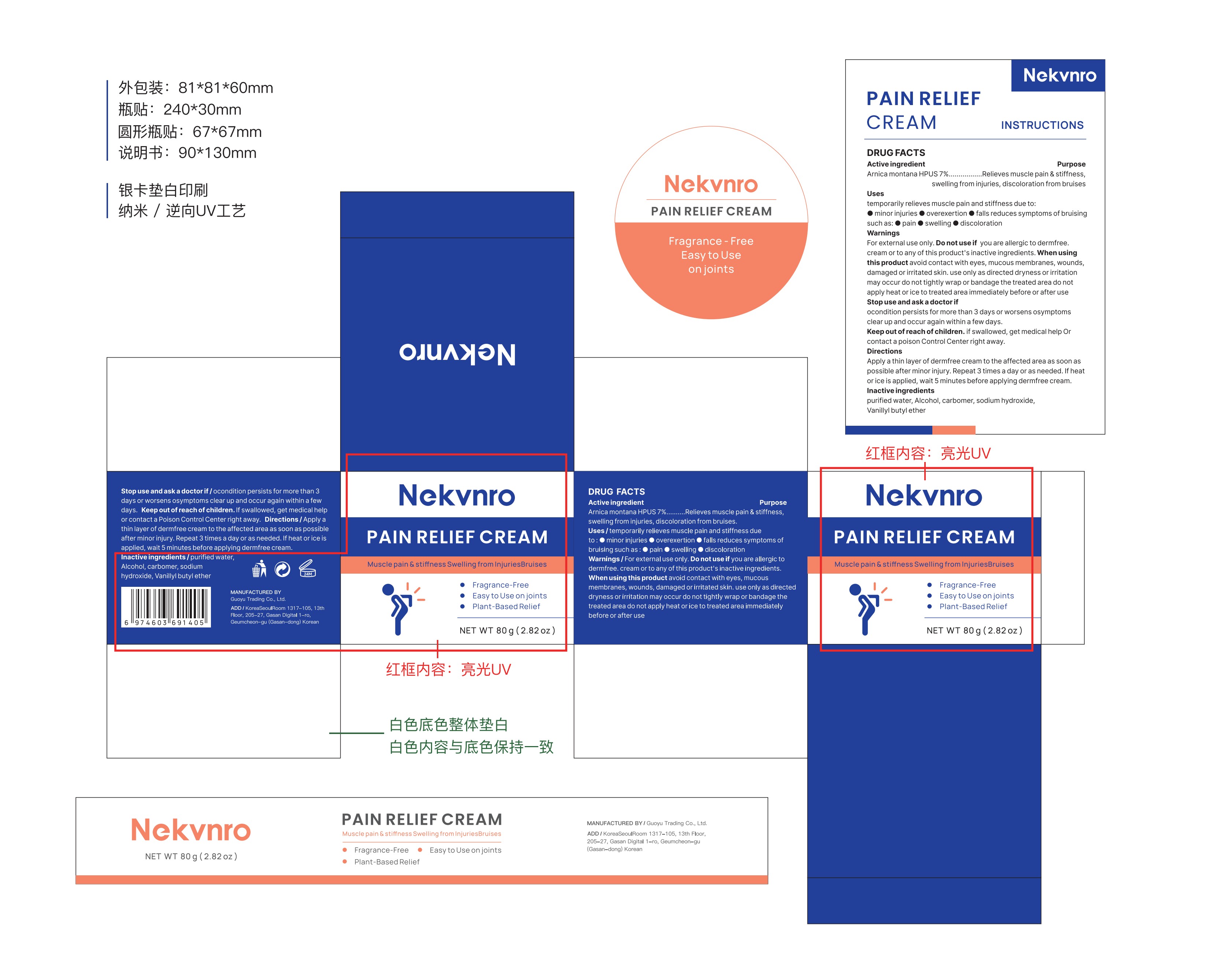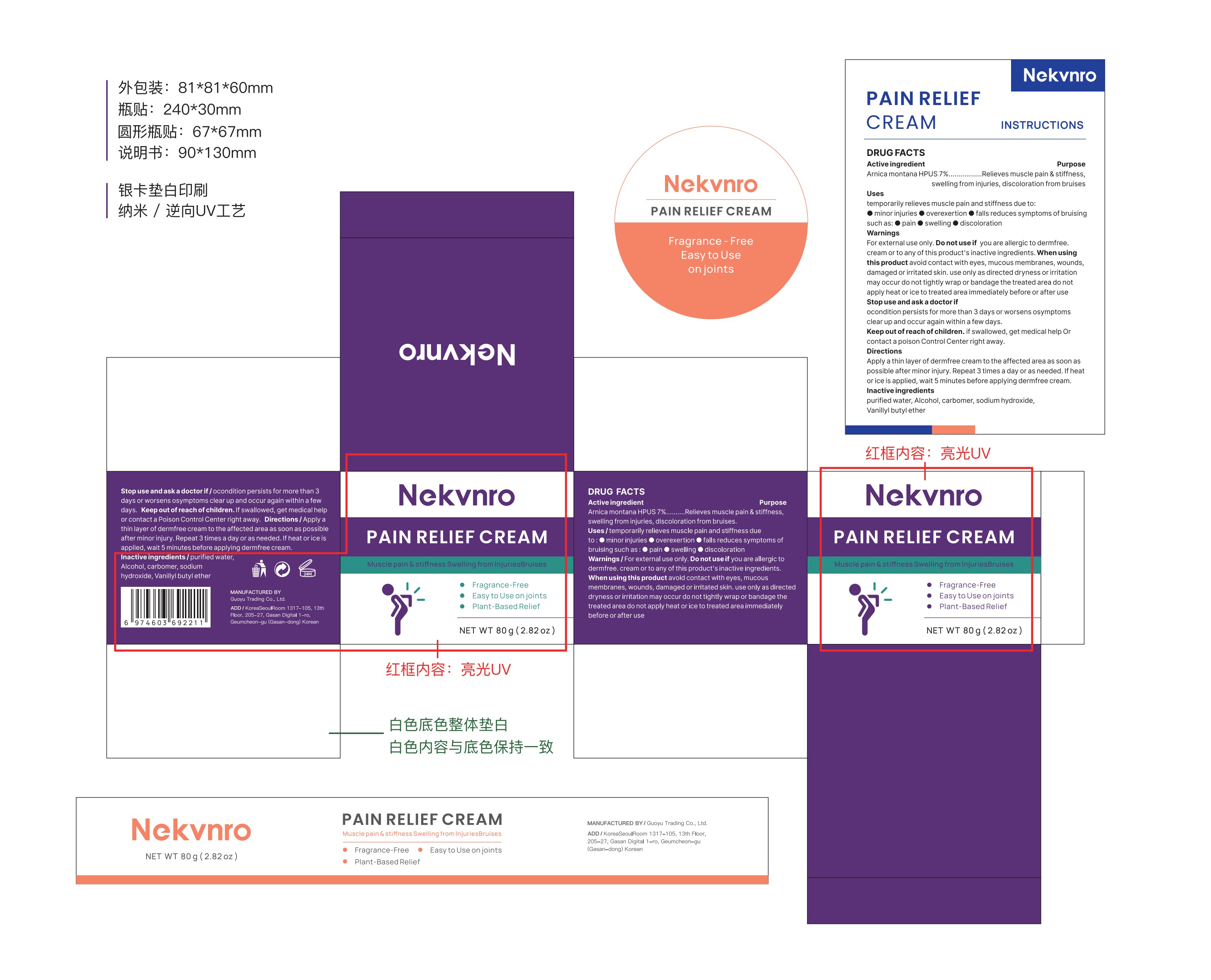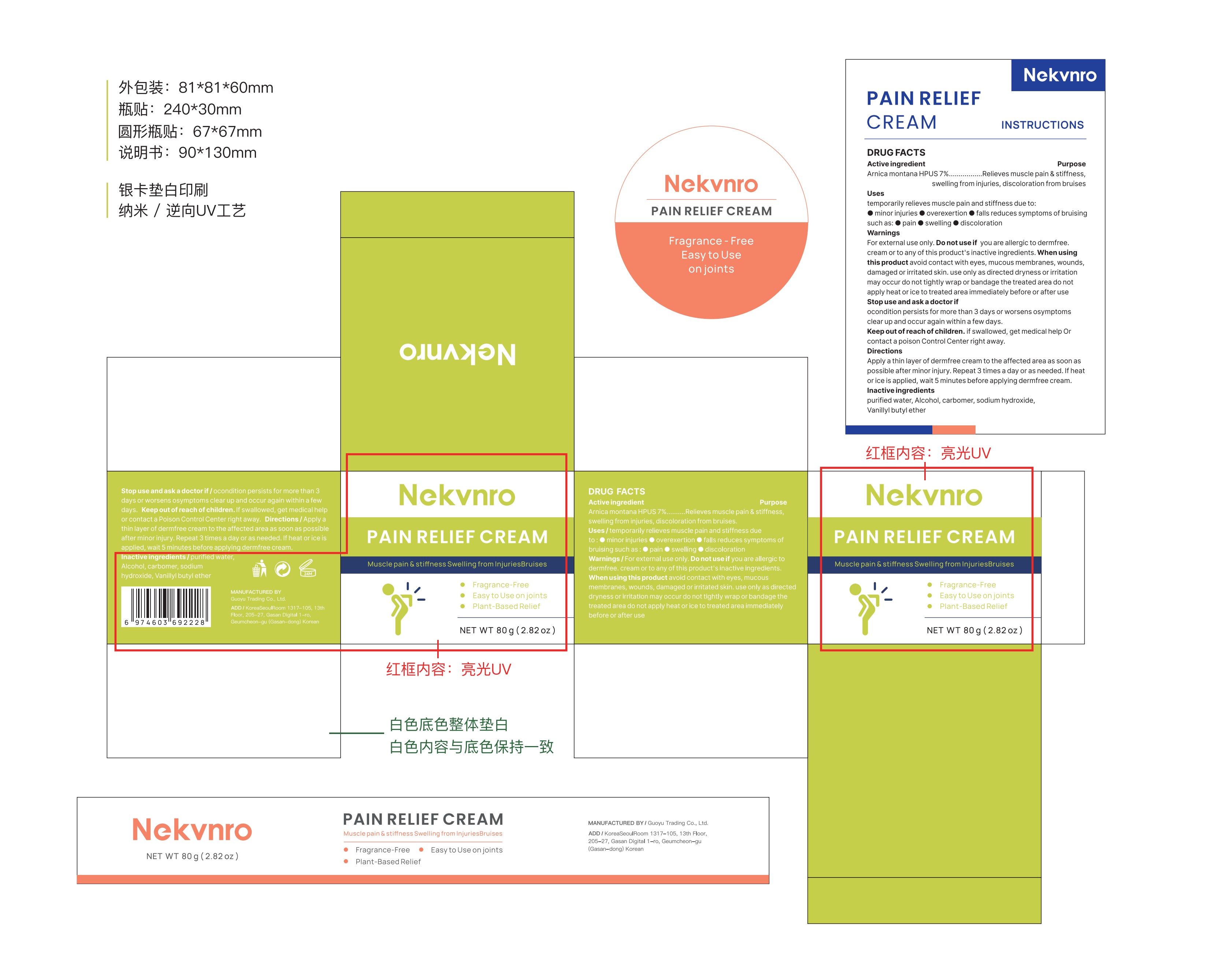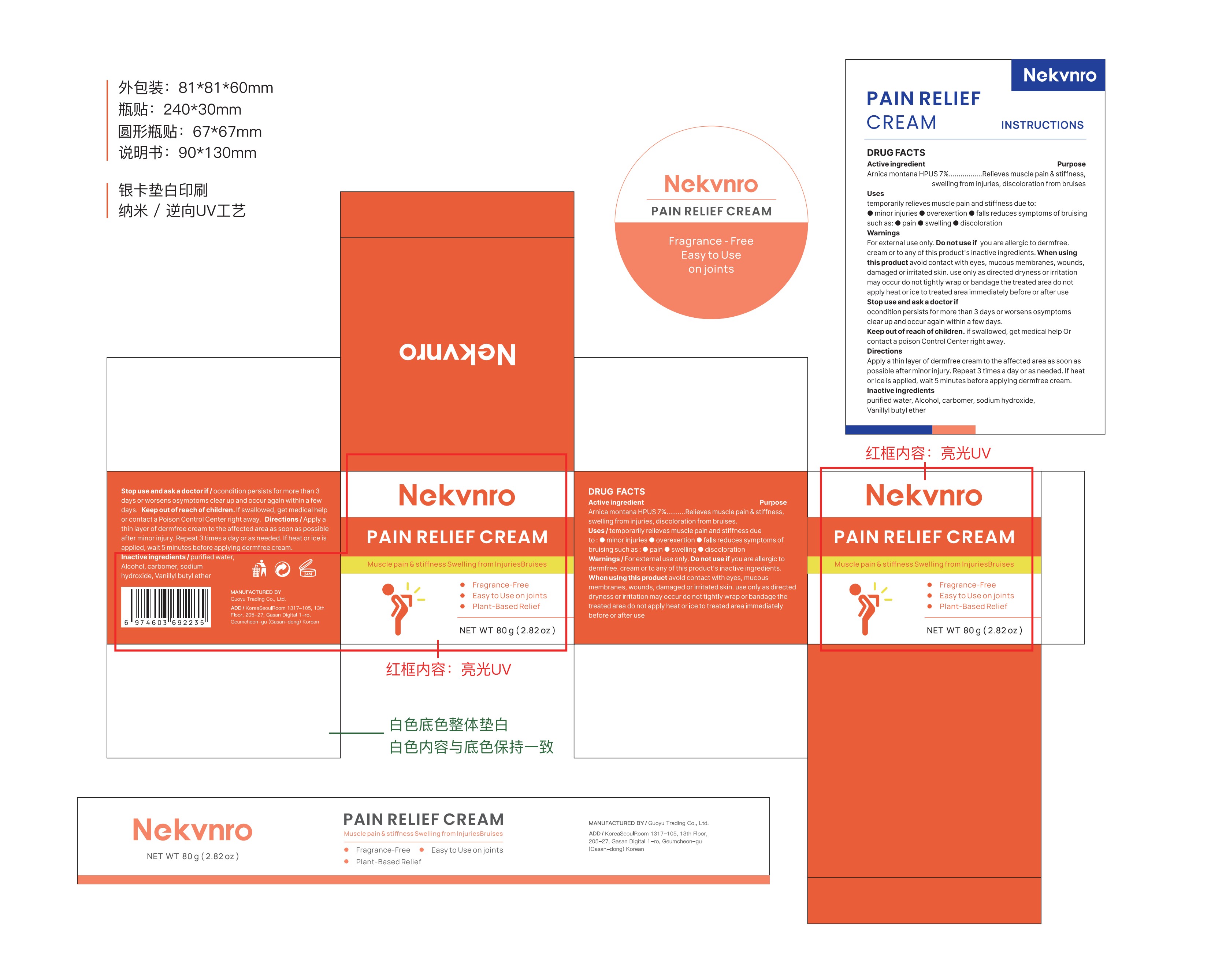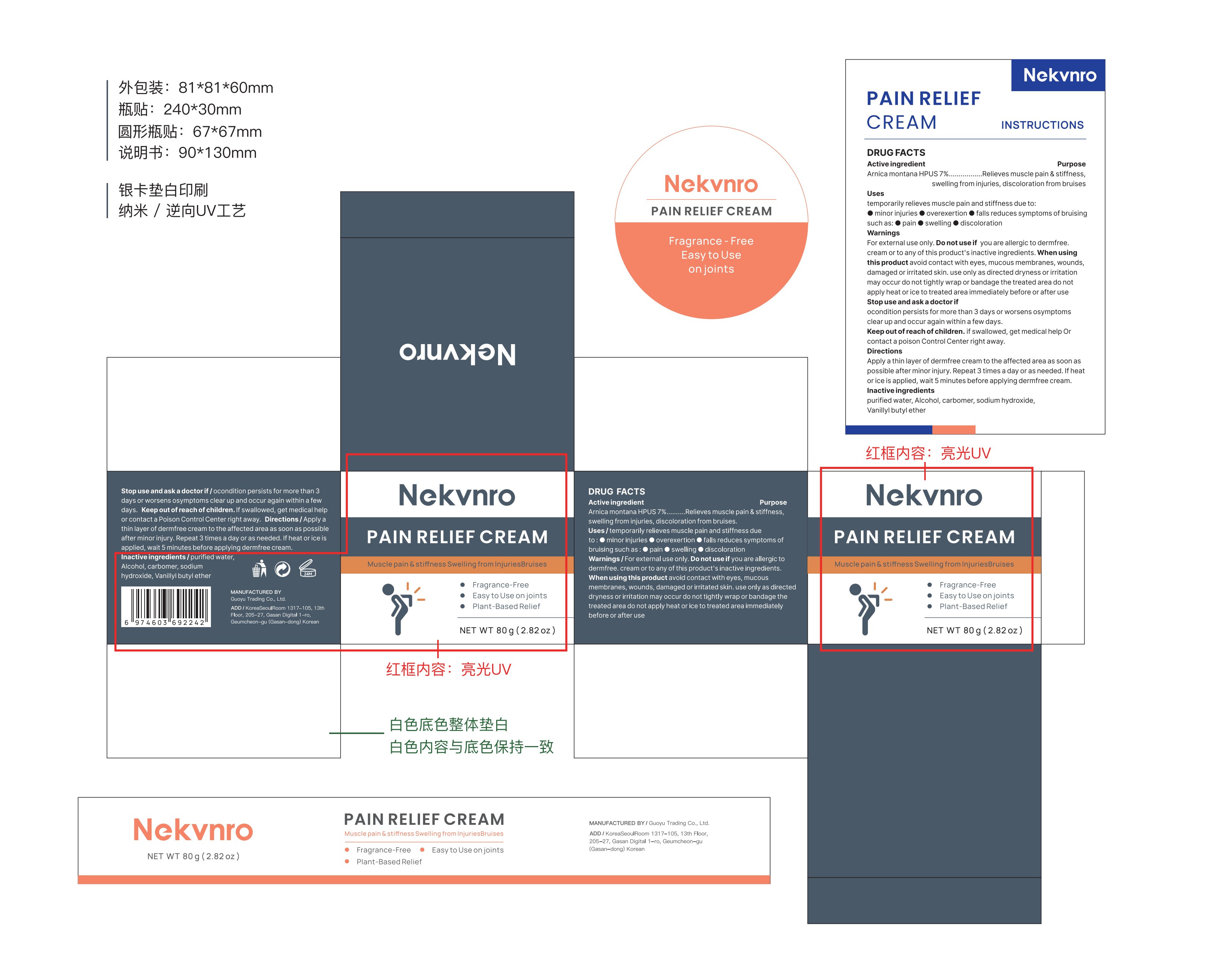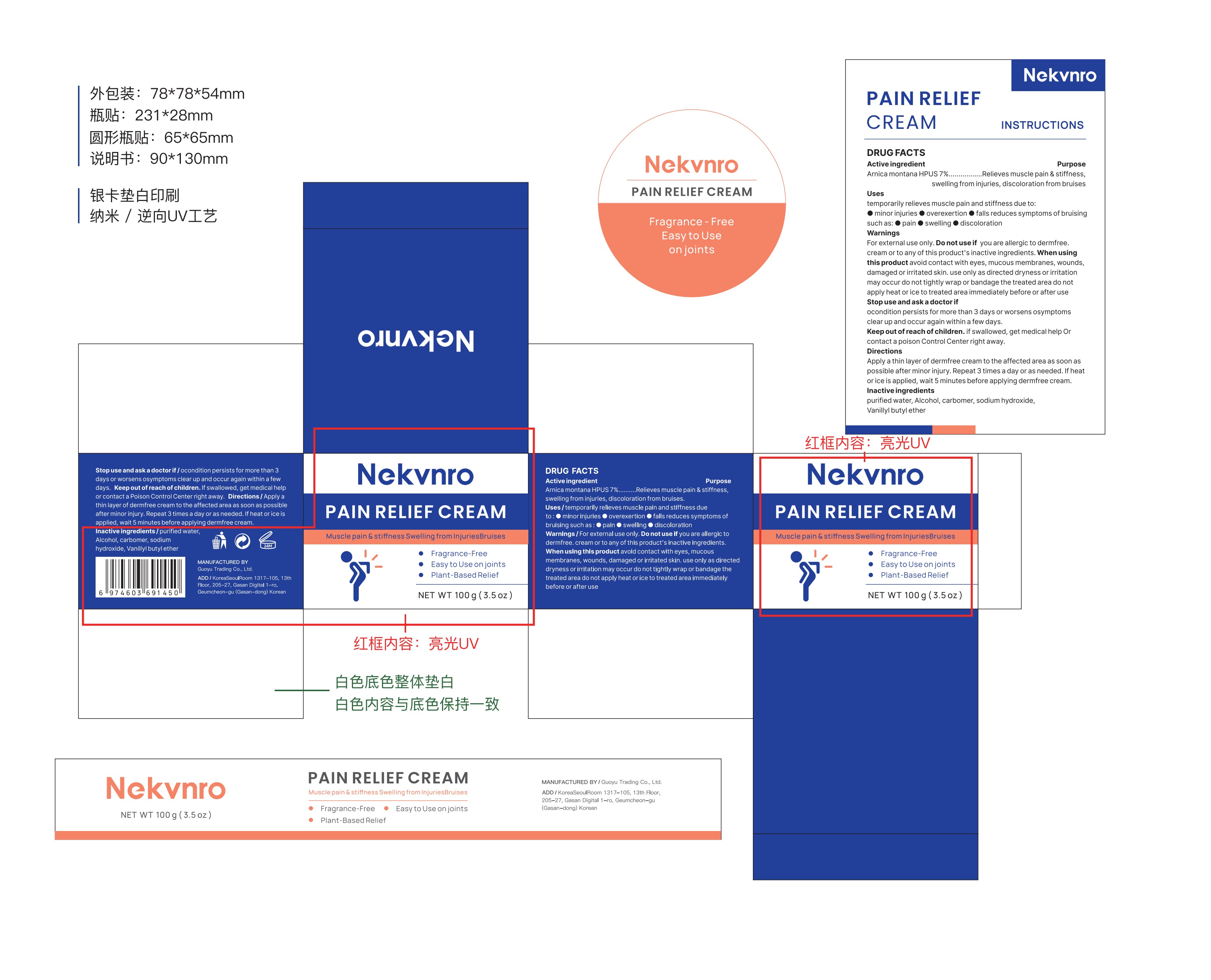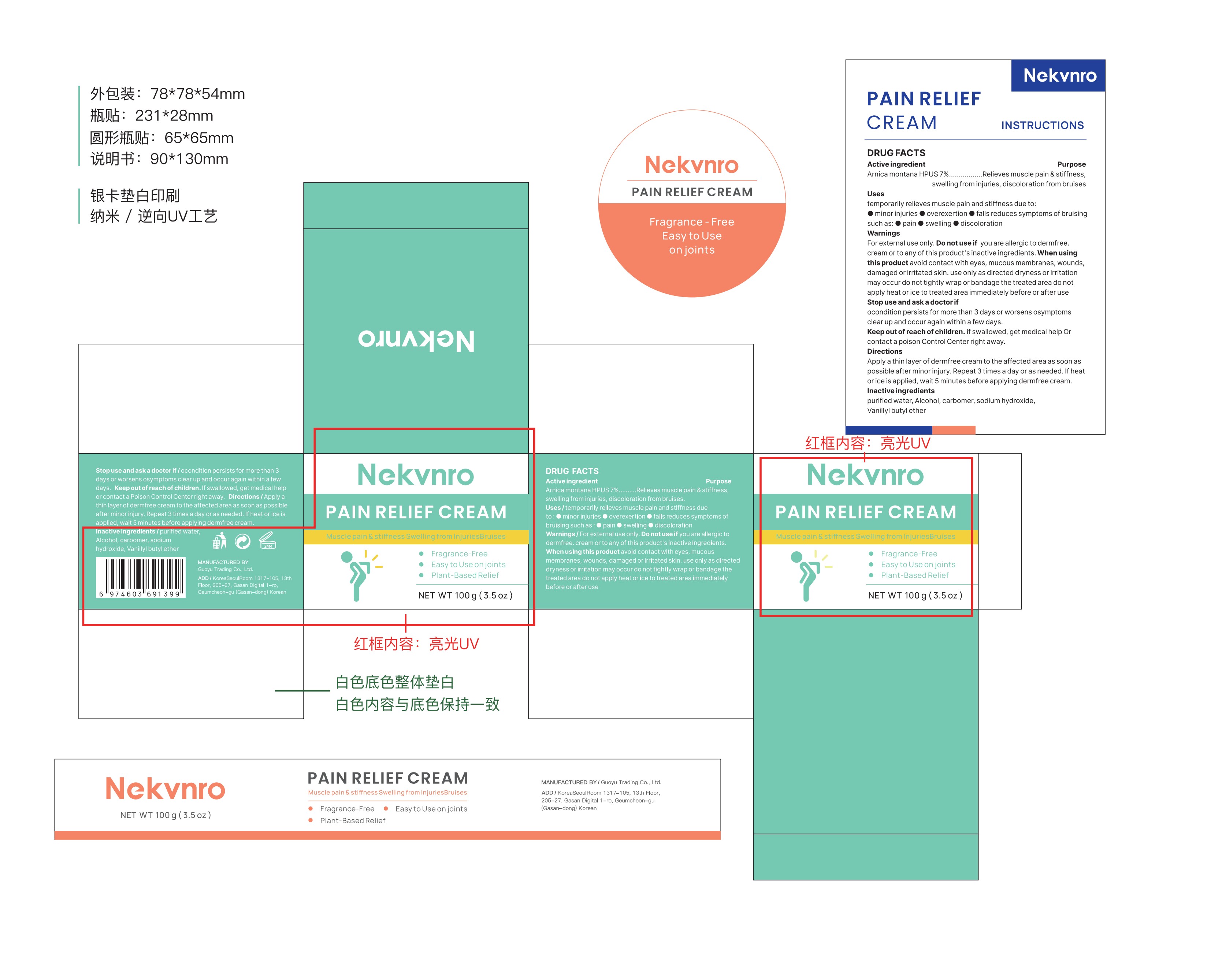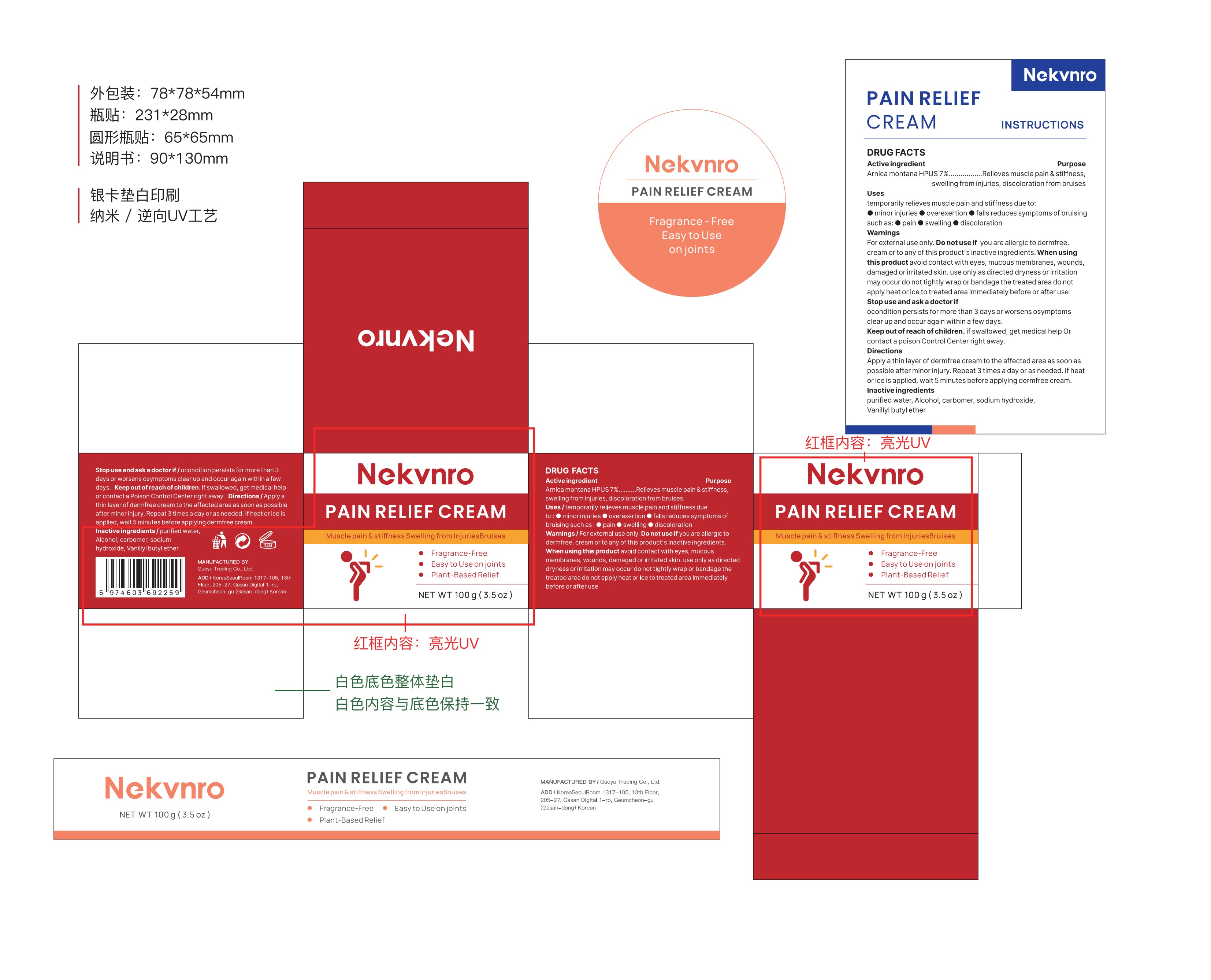 DRUG LABEL: Nekvnro Pain Relief Cream
NDC: 84844-003 | Form: CREAM
Manufacturer: Guoyu Trading Co., Ltd.
Category: otc | Type: HUMAN OTC DRUG LABEL
Date: 20241023

ACTIVE INGREDIENTS: ARNICA MONTANA 7 g/100 g
INACTIVE INGREDIENTS: ALCOHOL; SODIUM HYDROXIDE; WATER; CARBOMER; VANILLYL BUTYL ETHER

84844-003

Active Ingredient

Arnica montana HPUS 7%

Purpose

Relieves muscle pain &stiffness, swelling from injuries, discoloration from bruises

Use

temporarily relieves muscle pain and stiffness due to：
■minor injuries

■overexertion

■falls reduces symptoms of bruising such as:

■pain ■swelling

■discoloration

Warnings

For external use only,Do not use if you are allergic to dermfree.cream or to any of this product's inactive ingredients

Do not use

if you are allergic to dermfree.cream or to any of this product's inactive ingredients

When Using

this product avoid contact with eyes, mucous membranes, wounds, damaged or irritated skin. use only as directed dryness or irritation may occur
do not tightly wrap or bandage the treated area
do not apply heat or ice to treated area immediately before or after use

Stop Use

ocondition persists for more than 3 days or worsens
osymptoms clear up and occur again within a few days.

Ask Doctor

ocondition persists for more than 3 days or worsens
osymptoms clear up and occur again within a few days.

Keep Oot Of Reach Of Children

if swallowed，get medical help Or contact a poison Control Center right away.

Directions

Apply a thin layer of dermfree cream to the affected area as soon as possible after minor injury. Repeat 3 times a day or as needed. If heat or ice is applied， wait 5 minutes before applying dermfree cream.

Inactive ingredients

purified water,Alcohol, carbomer,sodium hydroxide, Vanillyl butyl ether